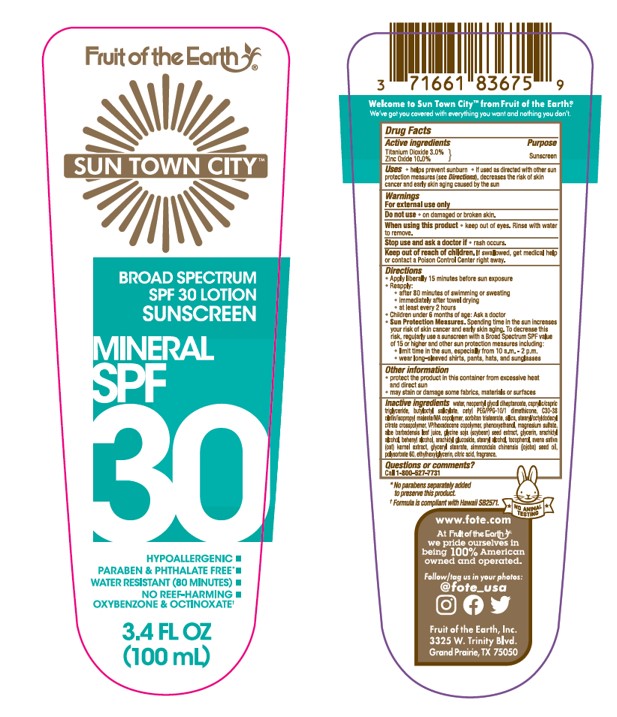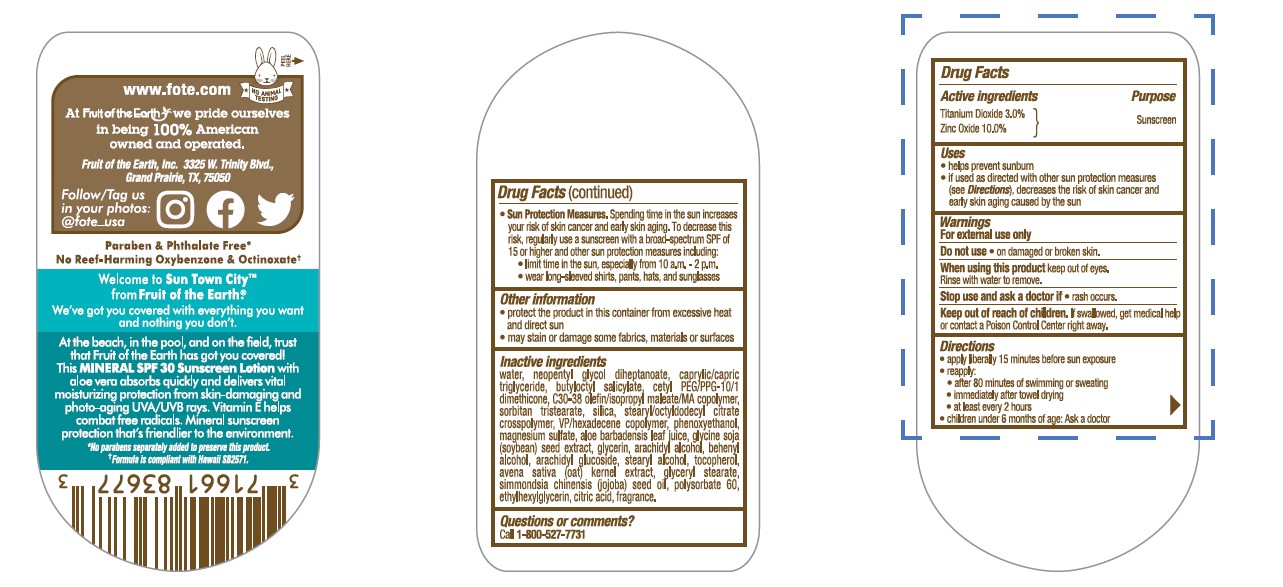 DRUG LABEL: Fruit of the Earth Sun Town City Mineral SPF 30 Sunscreen
NDC: 62217-243 | Form: LOTION
Manufacturer: Fruit Of The Earth, Inc.
Category: otc | Type: HUMAN OTC DRUG LABEL
Date: 20241018

ACTIVE INGREDIENTS: TITANIUM DIOXIDE 30 mg/1 mL; ZINC OXIDE 100 mg/1 mL
INACTIVE INGREDIENTS: POLYSORBATE 60; CETYL PEG/PPG-10/1 DIMETHICONE (HLB 5); ANHYDROUS CITRIC ACID; DOCOSANOL; MEDIUM-CHAIN TRIGLYCERIDES; JOJOBA OIL; ETHYLHEXYLGLYCERIN; PHENOXYETHANOL; SILICON DIOXIDE; ALOE VERA LEAF; GLYCERYL 1-STEARATE; STEARYL/OCTYLDODECYL CITRATE CROSSPOLYMER; .ALPHA.-TOCOPHEROL, DL-; OAT; MAGNESIUM SULFATE HEPTAHYDRATE; VINYLPYRROLIDONE/HEXADECENE COPOLYMER; ARACHIDYL ALCOHOL; WATER; GLYCERIN; SORBITAN TRISTEARATE; BUTYLOCTYL SALICYLATE; NEOPENTYL GLYCOL DIHEPTANOATE; SOYBEAN; STEARYL ALCOHOL; ARACHIDYL GLUCOSIDE

Fruit of the Earth Sun Town City Mineral SPF 30 Lotion Sunscreen

Active ingredients

Titanium Dioxide 3.0%

Zinc Oxide 10.0%

Purpose

Sunscreen

Uses

• helps prevent sunburn • if used as directed with other sun protection measures (see Directions), decreases the risk of skin cancer and early skin aging caused by the sun

Warnings

For external use only

Do not use

•on damaged or broken skin.

When using this product

• keep out of eyes. Rinse with water to remove.

Stop use and ask a doctor if

• rash occurs.

Keep out of reach of children

If product is swallowed, get medical help or contact a Poison Control Poison Control Center right away.

Directions

• apply liberally 15 minutes before sun exposure

• reapply:

• after 80 minutes of swimming or sweating

• immediately after towel drying

• at least every 2 hours

• children under 6 months of age: Ask a doctor

• Sun Protection Measures. Spending time in the sun increases your risk of skin cancer and early skin aging. To decrease this risk, regularly use a sunscreen with a Broad Spectrum SPF value of 15 or higher and other sun protection measures including:

• limit time in the sun, especially from 10 a.m. - 2 p.m.

• wear long-sleeved shirts, pants, hats, and sunglasses

Other information

• protect the product in this container from excessive heat and direct sun

• may stain or damage some fabrics, materials or surfaces

Inactive ingredients

water, neopentyl glycol diheptanoate, caprylic/capric triglyceride, butyloctyl salicylate, cetyl PEG/PPG-10/1 dimethicone, C30-38 olefin/isopropyl maleate/MA copolymer, sorbitan tristearate, silica, stearyl/octldodecyl citrate crosspolymer, VP/hexadecene copolymer, phenoxyethanol, magnesium sulfate, aloe barbadensis leaf juice, glycerine soja (soybean) seed extract, glycerin, arachidyl alcohol, behenyl alcohol, arachidyl glucoside, stearyl alcohol, tocopherol, avena sativa (oat) kernel extract, glyceryl stearate, simmondsia chinensis (jojoba) seed oil, polysorbate 60, ethylhexylglycerin, citric acid, fragrance.